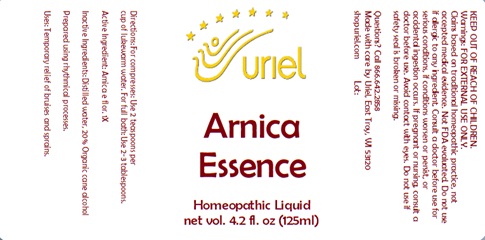 DRUG LABEL: Arnica Essence
NDC: 48951-8427 | Form: LIQUID
Manufacturer: Uriel Pharmacy Inc.
Category: homeopathic | Type: HUMAN OTC DRUG LABEL
Date: 20241211

ACTIVE INGREDIENTS: ARNICA MONTANA FLOWER 1 [hp_X]/1 mL
INACTIVE INGREDIENTS: WATER; ALCOHOL

Arnica Essence

INDICATIONS AND USAGE

Directions: For Compresses:

DOSAGE AND ADMINISTRATION

Use 2 teaspoons per cup of lukewarm water. For full bath: Use 2-3 tablespoons.

Active Ingredient: Arnica e flor. 1X

Inactive Ingredients: Distilled water, 20% Organic cane alcohol

Prepared using rhythmical processes.

PURPOSE

Uses: Temporary relief of bruises and sprains.

KEEP OUT OF REACH OF CHILDREN.

Warnings: FOR EXTERNAL USE ONLY.
Claims based on traditional homeopathic practice, not accepted medical evidence. Not FDA evaluated. Do not use if allergic to any ingredient. Consult a doctor before use for serious conditions, if conditions worsen or persist, or accidental ingestion occurs. If pregnant or nursing, consult a doctor before use. Avoid contact with eyes. Do not use if safety seal is broken or missing.

QUESTIONS

Questions? Call 866.642.2858 Made with care by Uriel, East Troy, WI 53120 shopuriel.com Lot: